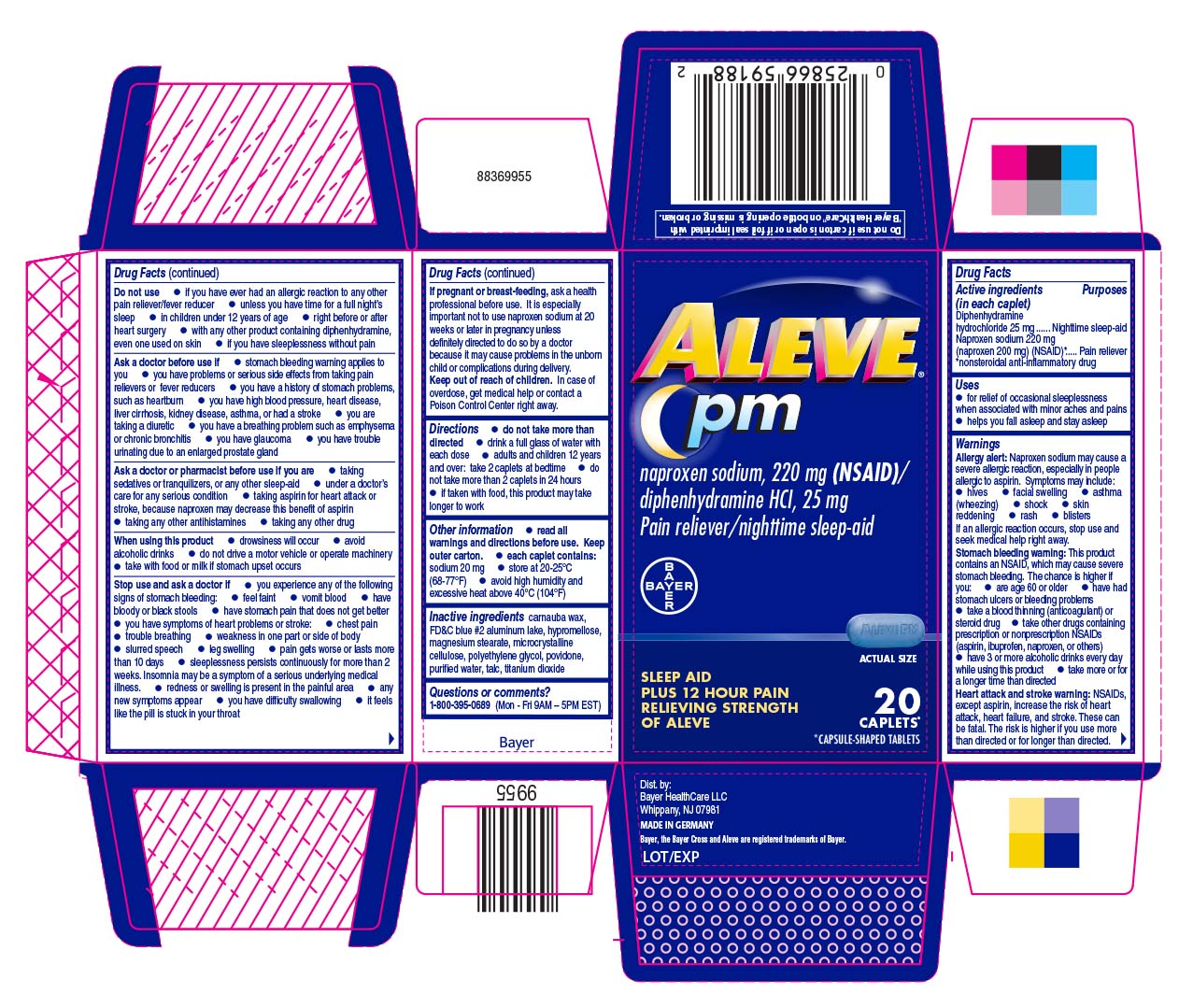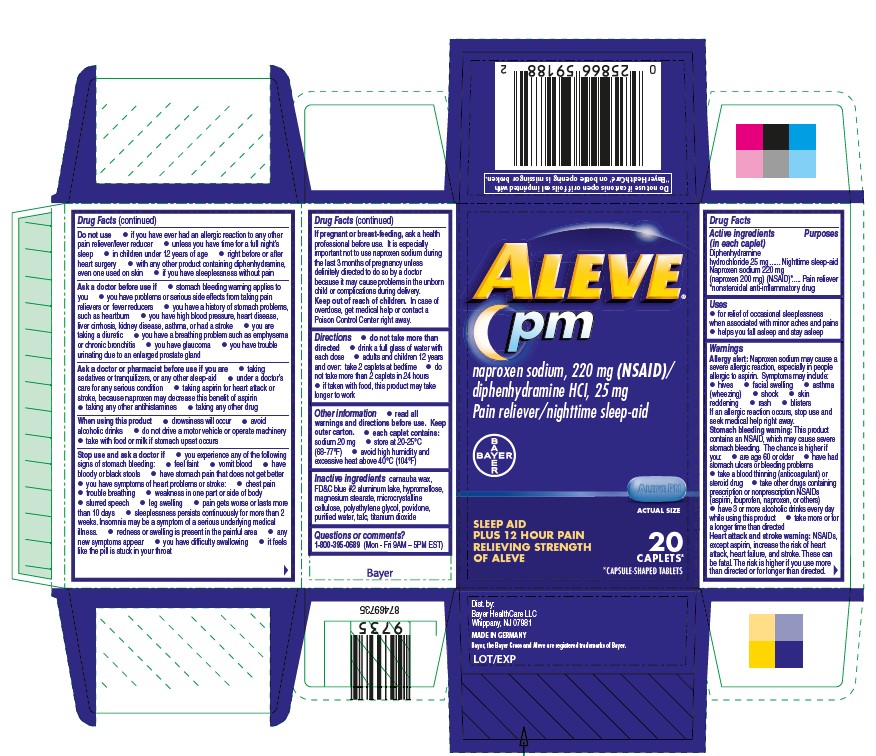 DRUG LABEL: Aleve PM
NDC: 0280-1200 | Form: TABLET, FILM COATED
Manufacturer: Bayer HealthCare LLC.
Category: otc | Type: HUMAN OTC DRUG LABEL
Date: 20251204

ACTIVE INGREDIENTS: DIPHENHYDRAMINE HYDROCHLORIDE 25 mg/1 1; NAPROXEN SODIUM 220 mg/1 1
INACTIVE INGREDIENTS: FD&C BLUE NO. 2; ALUMINUM OXIDE; HYPROMELLOSES; MAGNESIUM STEARATE; CELLULOSE, MICROCRYSTALLINE; POLYETHYLENE GLYCOL, UNSPECIFIED; CARNAUBA WAX; POVIDONE; WATER; TALC; TITANIUM DIOXIDE

Aleve® PM

Drug Facts

ACTIVE INGREDIENT

PURPOSE

Active ingredients (in each caplet) | Purposes
Diphenhydramine hydrochloride 25 mg | Nighttime sleep-aid
Naproxen sodium 220 mg (naproxen 200 mg) (NSAID) [nonsteroidal anti-inflammatory drug] | Pain reliever

Uses

- for relief of occasional sleeplessness when associated with minor aches and pains
- helps you fall asleep and stay asleep

WARNINGS

Warnings

Allergy alert

Naproxen sodium may cause a severe allergic reaction, especially in people allergic to aspirin. Symptoms may include:

- hives
- facial swelling
- asthma (wheezing)
- shock
- skin reddening
- rash
- blisters

If an allergic reaction occurs, stop use and seek medical help right away.

Stomach bleeding warning

This product contains an NSAID, which may cause severe stomach bleeding. The chance is higher if you:

- are age 60 or older
- have had stomach ulcers or bleeding problems
- take a blood thinning (anticoagulant) or steroid drug
- take other drugs containing prescription or nonprescription NSAIDs (aspirin, ibuprofen, naproxen, or others)
- have 3 or more alcoholic drinks every day while using this product
- take more or for a longer time than directed

Heart attack and stroke warning

NSAIDs, except aspirin, increase the risk of heart attack, heart failure, and stroke. These can be fatal. The risk is higher if you use more than directed or for longer than directed.

Do not use

- if you have ever had an allergic reaction to any other pain reliever/fever reducer
- unless you have time for a full night's sleep
- in children under 12 years of age
- right before or after heart surgery
- with any other product containing diphenhydramine, even one used on skin
- if you have sleeplessness without pain

Ask a doctor before use if

- stomach bleeding warning applies to you
- you have problems or serious side effects from taking pain relievers or fever reducers
- you have a history of stomach problems, such as heartburn
- you have high blood pressure, heart disease, liver cirrhosis, kidney disease, asthma or had a stroke
- you are taking a diuretic
- you have a breathing problem such as emphysema or chronic bronchitis
- you have glaucoma
- you have trouble urinating due to an enlarged prostate gland

Ask a doctor or pharmacist before use if you are

- taking sedatives or tranquilizers, or any other sleep-aid
- under a doctor's care for any serious condition
- taking aspirin for heart attack or stroke, because naproxen may decrease this benefit of aspirin
- taking any other antihistamines
- taking any other drug

When using this product

- drowsiness will occur
- avoid alcoholic drinks
- do not drive a motor vehicle or operate machinery
- take with food or milk if stomach upset occurs

Stop use and ask a doctor if

- you experience any of the following signs of stomach bleeding:
  - feel faint
  - vomit blood
  - have bloody or black stools
  - have stomach pain that does not get better
- you have symptoms of heart problems or stroke:
  - chest pain
  - trouble breathing
  - weakness in one part or side of body
  - slurred speech
  - leg swelling

- pain gets worse or lasts more than 10 days
- sleeplessness persists continuously for more than 2 weeks. Insomnia may be a symptom of a serious underlying medical illness.
- redness or swelling is present in the painful area
- any new symptoms appear
- you have difficulty swallowing
- it feels like the pill is stuck in your throat

PREGNANCY OR BREAST FEEDING

If pregnant or breast-feeding, ask a health professional before use. It is especially important not to use naproxen sodium 20 weeks or later in pregnancy unless definitely directed to do so by a doctor because it may cause problems in the unborn child or complications during delivery.

Keep out of reach of children. In case of overdose, get medical help or contact a Poison Control Center right away.

Directions

- do not take more than directed
- drink a full glass of water with each dose
- adults and children 12 years and over: take 2 caplets at bedtime
- do not take more than 2 caplets in 24 hours
- if taken with food, this product may take longer to work

Other information

- read all warnings and directions before use. Keep outer carton.
- each caplet contains: sodium 20 mg
- store at 20-25°C (68-77°F)
- avoid high humidity and excessive heat above 40°C (104°F)

Inactive ingredients

carnauba wax, FD&C blue #2 aluminum lake, hypromellose, magnesium stearate, microcrystalline cellulose, polyethylene glycol, povidone, purified water, talc, titanium dioxide

Questions or comments?

1-800-395-0689 (Mon – Fri 9AM – 5PM EST)

PRINCIPAL DISPLAY PANEL - 20 Tablet Bottle Carton

Aleve® PM

naproxen sodium, 220 mg (NSAID)/

diphenhydramine HCl, 25 mg

Pain reliever/nighttime sleep-aid

SLEEP AID PLUS

12 HOUR PAIN RELIEVING

STRENGTH OF ALEVE

ACTUAL SIZE

20 CAPLETS

*CAPSULE-SHAPED TABLETS